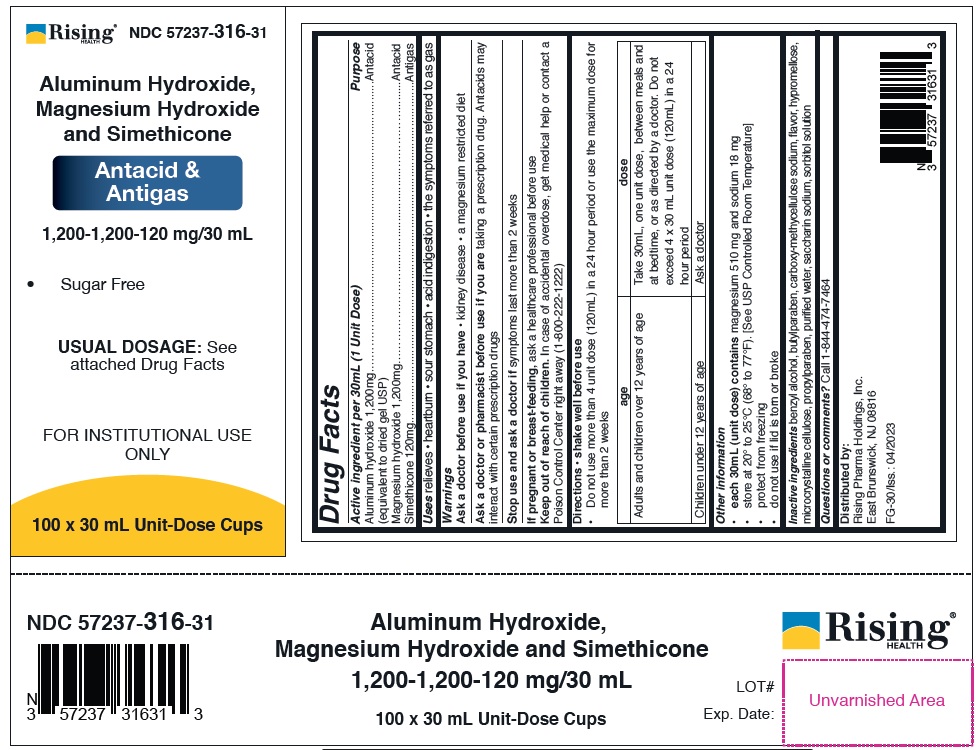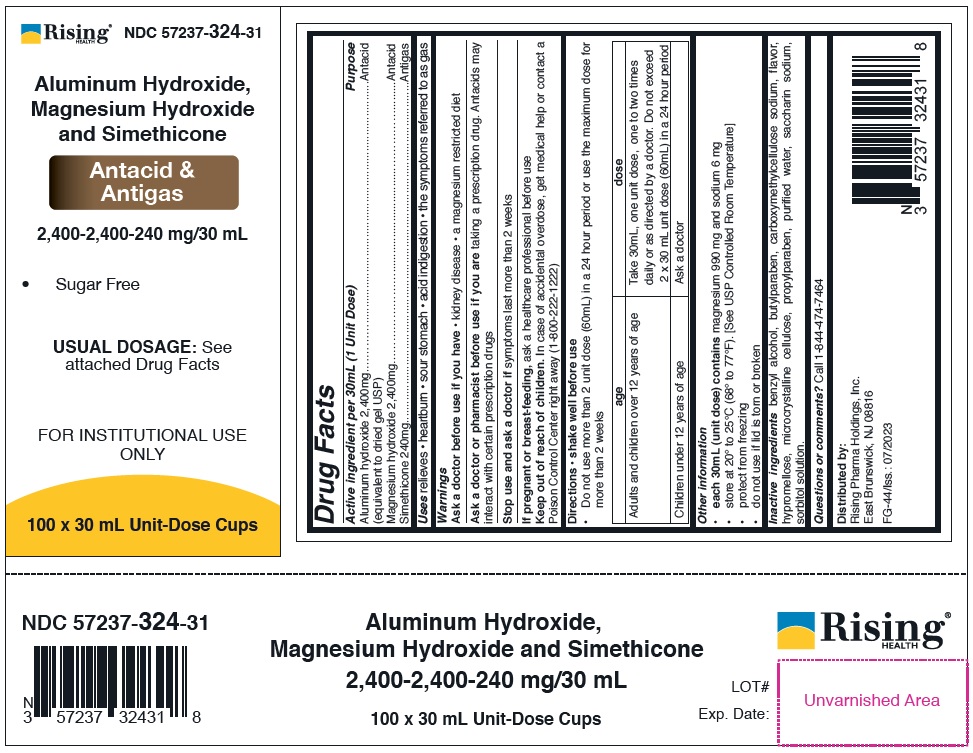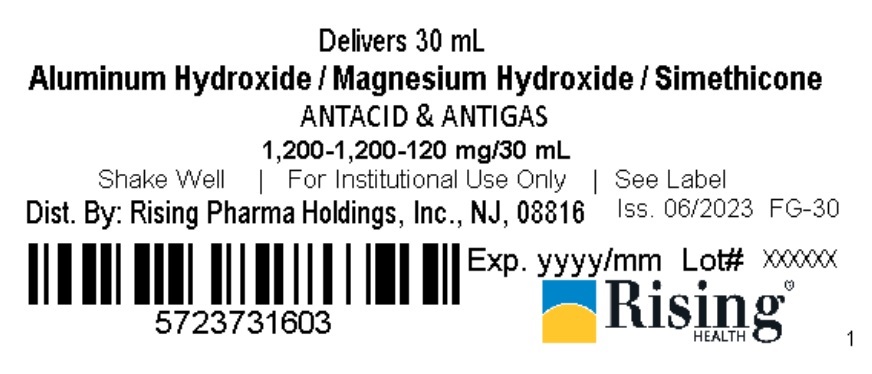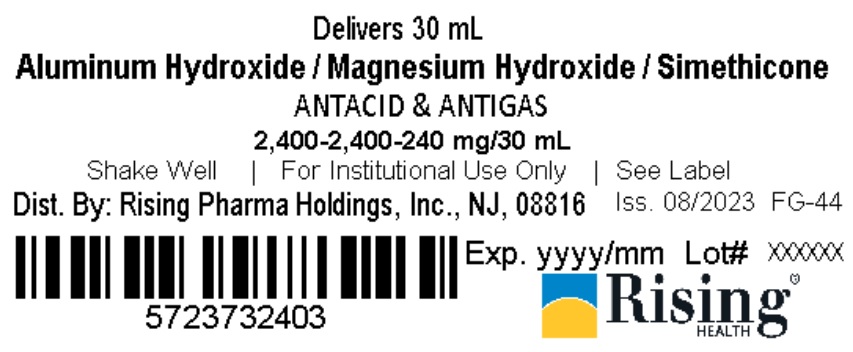 DRUG LABEL: Aluminum Hydroxide, Magnesium Hydroxide and Simethicone
NDC: 57237-316 | Form: SUSPENSION
Manufacturer: Rising Pharma Holdings, Inc.
Category: otc | Type: HUMAN OTC DRUG LABEL
Date: 20250701

ACTIVE INGREDIENTS: ALUMINUM HYDROXIDE 1200 mg/30 mL; MAGNESIUM HYDROXIDE 1200 mg/30 mL; DIMETHICONE 120 mg/30 mL
INACTIVE INGREDIENTS: BENZYL ALCOHOL; BUTYLPARABEN; CARBOXYMETHYLCELLULOSE SODIUM; HYPROMELLOSE, UNSPECIFIED; MICROCRYSTALLINE CELLULOSE; PROPYLPARABEN; WATER; SACCHARIN SODIUM; SORBITOL SOLUTION

Aluminum Hydroxide, Magnesium Hydroxide and Simethicone 1,200-1,200-120 mg/30 mL, 2,400-2,400-240 mg/30 mL

Drug Facts

ACTIVE INGREDIENT

PURPOSE

1,200-1,200-120 mg/30 mL

Active ingredient per 30mL (1 Unit Dose)
Aluminum hydroxide 1,200mg (equivalent to dried gel USP)
Magnesium hydroxide 1,200mg
Simethicone 120mg

2,400-2,400-240 mg/30 mL

Active ingredient per 30mL (1 Unit Dose)
Aluminum hydroxide 2,400mg (equivalent to dried gel USP)
Magnesium hydroxide 2,400mg
Simethicone 240mg

Purpose

Antacid

Antigas

Uses

relieves

• heartburn

• sour stomach

• acid indigestion

• the symptoms referred to as gas

Warnings

Ask a doctor before use if you have

• kidney disease

• a magnesium restricted diet

Ask a doctor or pharmacist before use if you are taking a prescription drug. Antacids may interact with certain prescription drugs

Stop use and ask a doctor if symptoms last more than 2 weeks

PREGNANCY OR BREAST FEEDING

If pregnant or breast-feeding, ask a healthcare professional before use

Keep out of reach of children. In case of accidental overdose, get medical help or contact a Poison Control Center right away (1-800-222-1222)

Directions • shake well before use

1,200-1,200-120 mg/30 mL

• Do not use more than 4 unit dose (120 mL) in a 24 hour period or use the maximum dose for more than 2 weeks

age | dose
Adults and children over 12 years of age | Take 30 mL, one unit dose, between meals and at bedtime, or as directed by a doctor. Do not exceed 4 x 30 mL unit dose (120 mL) in a 24 hour period
Children under 12 years of age | Ask a doctor

2,400-2,400-240 mg/30 mL

• Do not use more than 2 unit dose (60 mL) in a 24 hour period or use the maximum dose for more than 2 weeks

age | dose
Adults and children over 12 years of age | Take 30 mL, one unit dose, one to two times daily or as directed by a doctor. Do not exceed 2 x 30 mL unit dose (60 mL) in a 24 hour period
Children under 12 years of age | Ask a doctor

Other information

1,200-1,200-120 mg/30 mL

• each 30 mL (unit dose) contains magnesium 510 mg and sodium 18 mg

• store at 20° to 25°C (68° to 77°F). [See USP Controlled Room Temperature]

• protect from freezing

• do not use if lid is torn or broke

2,400-2,400-240 mg/30 mL

• each 30 mL (unit dose) contains magnesium 990 mg and sodium 6 mg

• store at 20° to 25°C (68° to 77°F). [See USP Controlled Room Temperature]

• protect from freezing

• do not use if lid is torn or broken

INACTIVE INGREDIENT

1,200-1,200-120 mg/30 mL / 2,400-2,400-240 mg/30 mL

Inactive ingredients benzyl alcohol, butylparaben, carboxy-methycellulose sodium, flavor, hypromellose, microcrystalline cellulose, propylparaben, purified water, saccharin sodium, sorbitol solution

QUESTIONS

NDC Information -

1,200-1,200-120 mg/30 mL

Each 30 mL of Aluminium Hydroxide / Magensium Hydroxide / Simethicone contains Aluminum hydroxide 1,200 mg, Magnesium hydroxide 1,200 mg and Simethicone 120 mg and is supplied in the following oral dosage forms:

NDC 57237-316-03 unit dose cup 30 mL
NDC 57237-316-31 (100 x 30 mL) unit-dose cups

2,400-2,400-240 mg/30 mL

Each 30 mL of Aluminium Hydroxide / Magensium Hydroxide / Simethicone contains Aluminum hydroxide 2,400 mg, Magnesium hydroxide 2,400 mg and Simethicone 240 mg and is supplied in the following oral dosage forms:

NDC 57237-324-03 unit dose cup 30 mL
NDC 57237-324-31 (100 x 30 mL) unit-dose cups

PACKAGE LABEL.PRINCIPAL DISPLAY PANEL

1,200-1,200-120 mg/30 mL

Case Label NDC 57237-316-31

1,200-1,200-120 mg/30 mL

Lid Label NDC 57237-316-03

2,400-2,400-240 mg/30 mL

Case Label NDC 57237-324-31

2,400-2,400-240 mg/30 mL
Lid Label NDC 57237-324-03